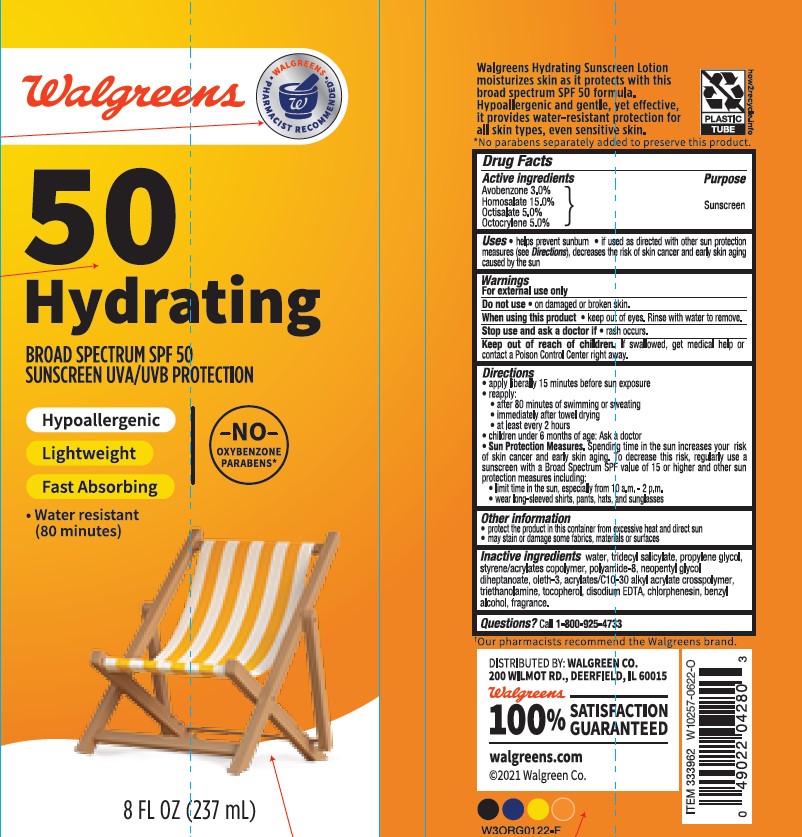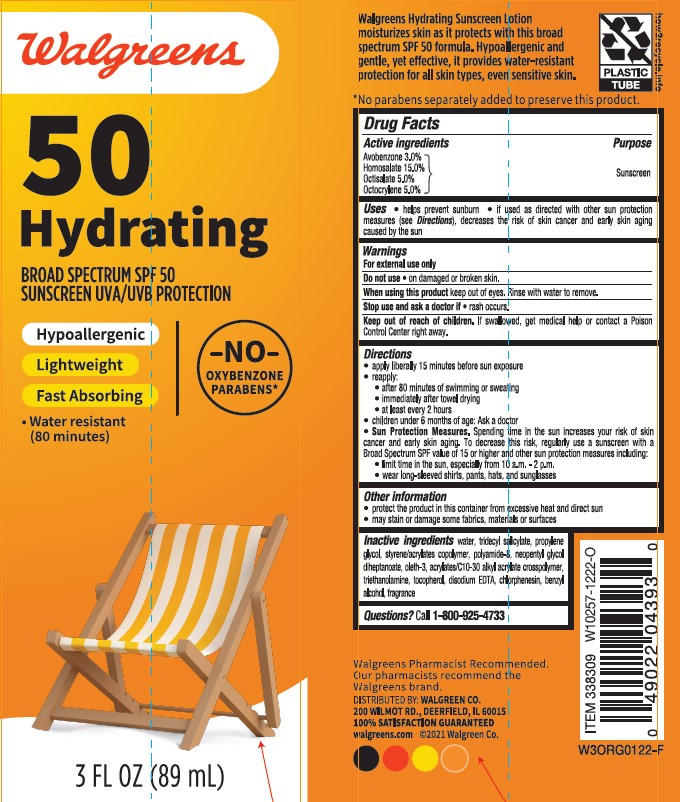 DRUG LABEL: Walgreens SPF 50 Hydrating
NDC: 0363-0136 | Form: LOTION
Manufacturer: WALGREEN COMPANY
Category: otc | Type: HUMAN OTC DRUG LABEL
Date: 20241222

ACTIVE INGREDIENTS: OCTOCRYLENE 50 mg/1 mL; OCTISALATE 50 mg/1 mL; HOMOSALATE 150 mg/1 mL; AVOBENZONE 30 mg/1 mL
INACTIVE INGREDIENTS: PROPYLENE GLYCOL; NEOPENTYL GLYCOL DIHEPTANOATE; CHLORPHENESIN; .ALPHA.-TOCOPHEROL, DL-; OLETH-3; BENZYL ALCOHOL; WATER; EDETATE DISODIUM; TRIDECYL SALICYLATE; TROLAMINE; POLYAMIDE-8 (4500 MW); CARBOMER COPOLYMER TYPE A; BUTYL METHACRYLATE/METHYL METHACRYLATE/METHACRYLIC ACID/STYRENE CROSSPOLYMER

Walgreens SPF 50 Hydrating Lotion

Active ingredients

Avobenzone 3.0%, Homosalate 15.0%, Octisalate 5.0%, Octocrylene 5.0%

Purpose

Sunscreen

Uses

• helps prevent sunburn

• if used as directed with other sun protection measures (see Directions),

decreases the risk of skin cancer and early skin aging caused by the sun

Warnings

For external use only

Do not use

• on damaged or broken skin.

When using this product

keep out of eyes. Rinse with water to remove.

Stop use and ask a doctor if

• rash occurs.

Keep out of reach of children.

If swallowed, get medical help or contact a Poison Control Center right away.

Directions

• apply liberally 15 minutes before sun exposure

reapply:

• after 80 minutes of swimming or sweating

• immediately after towel drying

• at least every 2 hours

• children under 6 months of age: Ask a doctor

Sun Protection Measures. Spending time in the sun increases

your risk of skin cancer and early skin aging. To decrease this

risk, regularly use a sunscreen with a Broad Spectrum SPF value

of 15 or higher and other sun protection measures including:

• limit time in the sun, especially from 10 a.m. - 2 p.m.

• wear long-sleeved shirts, pants, hats, and sunglasses

Other information

• protect the product in this container from excessive heat and direct sun

• may stain or damage some fabrics, materials or surfaces

Inactive ingredients

water, tridecyl salicylate, propylene glycol, styrene/acrylates copolymer, polyamide-8, neopentyl glycol diheptanoate, oleth-3, acrylates/C10-30 alkyl acrylate crosspolymer, triethanolamine, tocopherol, disodium EDTA, chlorphenesin, benzyl alcohol, fragrance